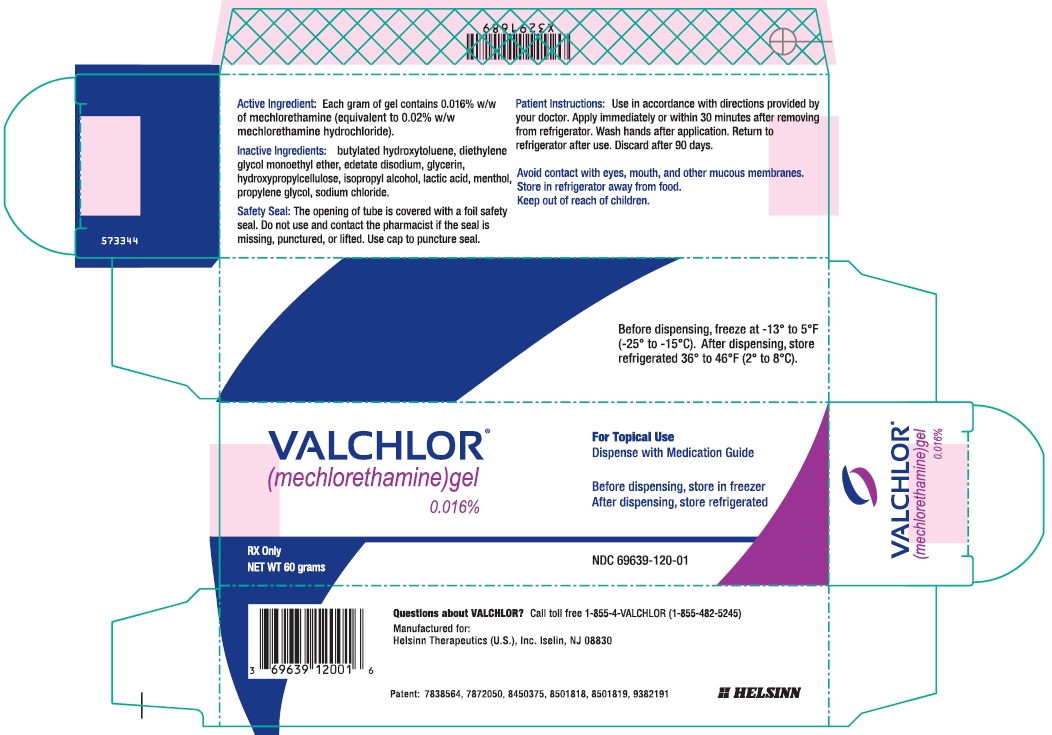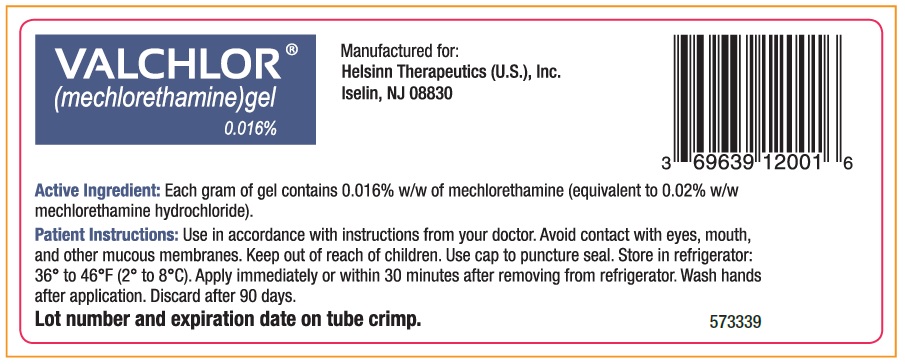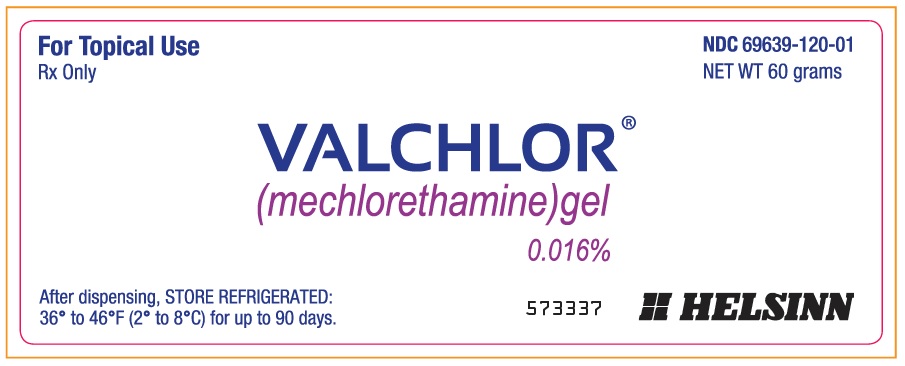 DRUG LABEL: VALCHLOR
NDC: 69639-120 | Form: GEL
Manufacturer: Helsinn Therapeutics (U.S.), Inc.
Category: prescription | Type: HUMAN PRESCRIPTION DRUG LABEL
Date: 20241120

ACTIVE INGREDIENTS: MECHLORETHAMINE 0.012 g/60 g
INACTIVE INGREDIENTS: DIETHYLENE GLYCOL MONOETHYL ETHER; PROPYLENE GLYCOL; ISOPROPYL ALCOHOL; GLYCERIN; LACTIC ACID, UNSPECIFIED FORM; HYDROXYPROPYL CELLULOSE (1600000 WAMW); SODIUM CHLORIDE; RACEMENTHOL; EDETATE DISODIUM; BUTYLATED HYDROXYTOLUENE

HIGHLIGHTS OF PRESCRIBING INFORMATION

These highlights do not include all the information needed to use VALCHLOR® safely and effectively. See full prescribing information for VALCHLOR.
VALCHLOR (mechlorethamine) gel, for topical use
Initial U.S. Approval: 1949

1 INDICATIONS AND USAGE

VALCHLOR is an alkylating drug indicated for the topical treatment of Stage IA and IB mycosis fungoides-type cutaneous T-cell lymphoma in patients who have received prior skin-directed therapy (1).

2 DOSAGE AND ADMINISTRATION

- For topical dermatological use only (2.1).
- Apply a thin film once daily to affected areas of the skin (2.1, 2.2).

3 DOSAGE FORMS AND STRENGTHS

Gel: 0.016% w/w of mechlorethamine (equivalent to 0.02% mechlorethamine HCl) in 60g tubes (3)

4 CONTRAINDICATIONS

Severe hypersensitivity to mechlorethamine (4)

5 WARNINGS AND PRECAUTIONS

- Mucosal or eye injury: VALCHLOR exposure to mucous membranes, especially of the eyes, can cause mucosal injury which may be severe. Eye injury may lead to blindness. Immediately irrigate for at least 15 minutes followed by immediate medical consultation (5.1).
- Secondary exposure to VALCHLOR: individuals other than the patient must avoid skin contact with VALCHLOR (2.2, 5.2).
- Dermatitis: Monitor patients for redness, swelling, inflammation, itchiness, blisters, ulceration, and secondary skin infections. Stop treatment or reduce dose frequency (2.1, 5.3).
- Non-melanoma skin cancer: Monitor patients during and after treatment (5.4).
- Embryo-fetal toxicity: May cause fetal harm (5.5).
- Flammable gel: VALCHLOR is an alcohol-based gel. Avoid fire, flame, and smoking until the gel has dried (2.2, 5.6).

6 ADVERSE REACTIONS

The most common adverse reactions (≥5%) are dermatitis, pruritus, bacterial skin infection, skin ulceration or blistering, and hyperpigmentation (6.1).

To report SUSPECTED ADVERSE REACTIONS, contact Helsinn Therapeutics (U.S.), Inc., at 1-855-482-5245 or FDA at 1-800-FDA-1088 or www.fda.gov/medwatch.

8 USE IN SPECIFIC POPULATIONS

Lactation: Advise not to breastfeed (8.2).

FULL PRESCRIBING INFORMATION

1 INDICATIONS AND USAGE

VALCHLOR is indicated for the topical treatment of Stage IA and IB mycosis fungoides-type cutaneous T-cell lymphoma in patients who have received prior skin-directed therapy.

2 DOSAGE AND ADMINISTRATION

2.1 Dosing and Dose Modification

For Topical Dermatological Use Only

Apply a thin film of VALCHLOR gel once daily to affected areas of the skin.

Stop treatment with VALCHLOR for any grade of skin ulceration, blistering, or moderately-severe or severe dermatitis (i.e., marked skin redness with edema) [see Warnings and Precautions (5.3)]. Upon improvement, treatment with VALCHLOR can be restarted at a reduced frequency of once every 3 days. If reintroduction of treatment is tolerated for at least one week, the frequency of application can be increased to every other day for at least one week and then to once daily application if tolerated.

2.2 Application Instructions

VALCHLOR is a cytotoxic drug. Follow applicable special handling and disposal procedures.^1

Patients must wash hands thoroughly with soap and water after handling or applying VALCHLOR.

Caregivers must wear disposable nitrile gloves when applying VALCHLOR to patients and wash hands thoroughly with soap and water after removal of gloves. If there is accidental skin exposure to VALCHLOR, caregivers must immediately wash exposed areas thoroughly with soap and water for at least 15 minutes and remove contaminated clothing [see Warnings and Precautions (5.2)].

Patients or caregivers should follow these instructions when applying VALCHLOR:

- Apply immediately or within 30 minutes after removal from the refrigerator. Return VALCHLOR to the refrigerator immediately after each use.
- Apply to completely dry skin at least 4 hours before or 30 minutes after showering or washing. Allow treated areas to dry for 5 to 10 minutes after application before covering with clothing.
- Emollients (moisturizers) may be applied to the treated areas 2 hours before or 2 hours after application.
- Do not use occlusive dressings on areas of the skin where VALCHLOR was applied.
- Avoid fire, flame, and smoking until VALCHLOR has dried [see Warnings and Precautions (5.6)].

3 DOSAGE FORMS AND STRENGTHS

The active ingredient in VALCHLOR is mechlorethamine. Each tube of VALCHLOR contains 60g of 0.016% w/w mechlorethamine clear gel (equivalent to 0.02% mechlorethamine HCl).

4 CONTRAINDICATIONS

The use of VALCHLOR is contraindicated in patients with known severe hypersensitivity to mechlorethamine. Hypersensitivity reactions, including anaphylaxis, have occurred with topical formulations of mechlorethamine.

5 WARNINGS AND PRECAUTIONS

5.1 Mucosal or Eye Injury

Exposure of the eyes to mechlorethamine causes pain, burns, inflammation, photophobia, and blurred vision. Blindness and severe irreversible anterior eye injury may occur. Advise patients that if eye exposure occurs, (1) immediately irrigate for at least 15 minutes with copious amounts of water, normal saline, or a balanced salt ophthalmic irrigating solution and (2) obtain immediate medical care (including ophthalmologic consultation).

Exposure of mucous membranes such as the oral mucosa or nasal mucosa causes pain, redness, and ulceration, which may be severe. Should mucosal contact occur, immediately irrigate for at least 15 minutes with copious amounts of water, followed by immediate medical consultation.

5.2 Secondary Exposure to VALCHLOR

Avoid direct skin contact with VALCHLOR in individuals other than the patient. Risks of secondary exposure include dermatitis, mucosal injury, and secondary cancers. Follow recommended application instructions to prevent secondary exposure [see Dosage and Administration (2.2)].

5.3 Dermatitis

The most common adverse reaction was dermatitis, which occurred in 56% of the patients [see Adverse Reactions (6.1)]. Dermatitis was moderately severe or severe in 23% of patients. Monitor patients for redness, swelling, inflammation, itchiness, blisters, ulceration, and secondary skin infections. The face, genitalia, anus, and intertriginous skin are at increased risk of dermatitis. Follow dose modification instructions for dermatitis [see Dosage and Administration (2.1)].

5.4 Non-Melanoma Skin Cancer

Four percent (4%, 11/255) of patients developed a non-melanoma skin cancer during the clinical trial or during one year of post-treatment follow-up: 2% (3/128) of patients receiving VALCHLOR, and 6% (8/127) of patients receiving the mechlorethamine ointment comparator. Some of these non-melanoma skin cancers occurred in patients who had received prior therapies known to cause non-melanoma skin cancer. Monitor patients for non-melanoma skin cancers during and after treatment with VALCHLOR. Non-melanoma skin cancer may occur on any area of the skin, including untreated areas.

5.5 Embryo-fetal Toxicity

Based on case reports in humans, findings in animal reproduction studies, its mechanism of action, and genotoxicity findings, mechlorethamine may cause fetal harm. There are case reports of children born with malformations in pregnant women systemically administered mechlorethamine. Mechlorethamine was teratogenic and embryo-lethal after a single subcutaneous administration to animals. Advise women to avoid becoming pregnant while using VALCHLOR. If this drug is used during pregnancy or if the patient becomes pregnant while taking this drug, the patient should be apprised of the potential hazard to a fetus [see Use in Specific Populations (8.1)].

5.6 Flammable Gel

Alcohol-based products, including VALCHLOR, are flammable. Follow recommended application instructions [see Dosage and Administration (2.2)].

6 ADVERSE REACTIONS

The following clinically significant adverse reactions are discussed in greater detail in other sections of the prescribing information:

- Mucosal or eye injury [see Warnings and Precautions (5.1)]
- Secondary exposure to VALCHLOR [see Warnings and Precautions (5.2)]
- Dermatitis [see Warnings and Precautions (5.3)]
- Non-melanoma skin cancer [see Warnings and Precautions (5.4)]

6.1 Clinical Trials Experience

Because clinical trials are conducted under widely varying conditions, adverse reaction rates observed in the clinical trials of a drug cannot be directly compared with rates in the clinical trials of another drug and may not reflect the rates observed in clinical practice.

In a randomized, observer-blinded, controlled trial, VALCHLOR 0.016% (equivalent to 0.02% mechlorethamine HCl) was compared to an Aquaphor®-based mechlorethamine HCl 0.02% ointment (Comparator) [see Clinical Studies (14)]. The maximum duration of treatment was 12 months. Sixty-three percent (63%) of patients in the VALCHLOR arm and 67% in the comparator arm completed 12 months of treatment.

The body system associated with the most frequent adverse reactions was skin and subcutaneous tissue disorders. The most common adverse reactions (occurring in at least 5% of the patients) are shown in Table 1.

Table 1. Most Commonly Reported (≥5%) Cutaneous Adverse Reactions
 | VALCHLOR N=128 % of patients |  | Comparator N=127 % of patients
 | Any Grade | Moderately-Severe or Severe | Any Grade | Moderately-Severe or Severe
Dermatitis | 56 | 23 | 58 | 17
Pruritus | 20 | 4 | 16 | 2
Bacterial skin infection | 11 | 2 | 9 | 2
Skin ulceration or blistering | 6 | 3 | 5 | 2
Skin hyperpigmentation | 5 | 0 | 7 | 0

In the clinical trial, moderately-severe to severe skin-related adverse events were managed with treatment reduction, suspension, or discontinuation. Discontinuations due to adverse reactions occurred in 22% of patients treated with VALCHLOR and 18% of patients treated with the comparator. Sixty-seven percent (67%) of the discontinuations for adverse reactions occurred within the first 90 days of treatment. Temporary treatment suspension occurred in 34% of patients treated with VALCHLOR and 20% of patients treated with the comparator. Reductions in dosing frequency occurred in 23% of patients treated with VALCHLOR and 12% of patients treated with the comparator.

Reductions in hemoglobin, neutrophil count, or platelet count occurred in 13% of patients treated with VALCHLOR and 17% treated with Comparator.

7 DRUG INTERACTIONS

No drug interaction studies have been performed with VALCHLOR. Systemic exposure has not been observed with topical administration of VALCHLOR; therefore, systemic drug interactions are not likely.

8 USE IN SPECIFIC POPULATIONS

8.1 Pregnancy

Risk Summary

Based on case reports in humans, findings in animal reproduction studies, its mechanism of action, and genotoxicity findings, mechlorethamine may cause fetal harm.

Available published case reports in pregnant women receiving intravenous mechlorethamine demonstrate that mechlorethamine can cause major birth defects when a pregnant woman is systemically exposed. In animal reproduction studies, subcutaneous administration of mechlorethamine to pregnant rats and ferrets during organogenesis resulted in embryo‐fetal mortality, alterations to growth, and structural abnormalities. Based on limited available data with VALCHLOR use in pregnant women, if VALCHLOR is used during pregnancy or if the patient becomes pregnant while taking this drug, patient should be advised of the potential risk to the fetus.

The estimated background risk of major birth defects and miscarriage for the indicated population is unknown. All pregnancies have a background risk of birth defect, loss, or other adverse outcomes. In the U.S. general population, the estimated background risk of major birth defects and miscarriage in clinically recognized pregnancies is 2-4% and 15-20%, respectively.

Data

Human Data
The limited available data with VALCHLOR use in pregnant women does not show evidence of congenital malformation in newborns. Cases of newborns with congenital malformations have been reported in women who received systemic mechlorethamine during pregnancy.

Animal Data
Mechlorethamine caused fetal malformations in the rat and ferret when given as single subcutaneous injections of 1 mg/kg. Other findings in animals included embryo lethality and growth retardation when administered as a single subcutaneous injection.

8.2 Lactation

Risk Summary

There are no data on the presence of mechlorethamine or its metabolites in human milk, the effects of the drug on the breastfed child, or the effects of the drug on milk production. Because of the potential for topical or systemic exposure to VALCHLOR through exposure to the mother's skin and the potential for serious adverse reactions in the breastfed child from mechlorethamine, advise patients not to breastfeed during treatment with VALCHLOR.

8.3 Females and Males of Reproductive Potential

Contraception

Females

Advise female patients of reproductive potential to use effective contraception during treatment with VALCHLOR. A barrier method of contraception should be used to avoid direct exposure of reproductive organs to VALCHLOR.

Males

Based on genotoxicity findings, advise males with female partners of reproductive potential to use effective contraception during treatment with VALCHLOR [ see Nonclinical Toxicology (13.1)]. A barrier method of contraception should be used to avoid direct exposure of reproductive organs to VALCHLOR.

Infertility

Based on animal data, mechlorethamine may impair fertility in males and females [see Nonclinical Toxicology (13.1)]. The reversibility of the effect on fertility is unknown.

8.4 Pediatric Use

Safety and effectiveness in pediatric patients have not been established.

8.5 Geriatric Use

A total of 79 patients age 65 and older (31% of the clinical trial population) were treated with either VALCHLOR or the comparator in the clinical trial. Forty-four percent (44%) of patients age 65 or older treated with VALCHLOR achieved a CAILS response compared to 66% of patients below the age of 65. Seventy percent (70%) of patients age 65 and older experienced cutaneous adverse reactions and 38% discontinued treatment due to adverse reactions, compared to 58% and 14% in patients below the age of 65, respectively. Similar differences in discontinuation rates between age subgroups were observed in the comparator group.

11 DESCRIPTION

VALCHLOR is a topical product that contains mechlorethamine HCl, an alkylating drug. Mechlorethamine HCl is a white to off white solid that is very soluble in water and methanol, partially soluble in acetone, and generally not soluble in organic solvents.

Mechlorethamine HCl is designated chemically as 2-chloro- N-(2-chloroethyl)- N-methylethanamine hydrochloride. The molecular weight is 192.52 and the melting point is 108-111°C. The empirical formula is C5H11Cl2N•HCl, and the structural formula is: CH3N(CH2CH2Cl)2•HCl.

Each tube of VALCHLOR contains 60g of a gel containing 0.016% w/w of mechlorethamine (equivalent to 0.02% mechlorethamine HCl) in a base of the following inactive ingredients: diethylene glycol monoethyl ether, propylene glycol, isopropyl alcohol, glycerin, lactic acid, hydroxypropylcellulose, sodium chloride, menthol, edetate disodium, butylated hydroxytoluene.

12 CLINICAL PHARMACOLOGY

12.1 Mechanism of Action

Mechlorethamine, also known as nitrogen mustard, is an alkylating agent which inhibits rapidly proliferating cells.

12.3 Pharmacokinetics

Systemic exposure was undetectable after topical administration of VALCHLOR to patients. Blood samples were analyzed from 16 and 15 patients following treatment with VALCHLOR (mechlorethamine gel 0.016%) and an identical formulation consisting of mechlorethamine 0.032% w/w, respectively. For patients who received mechlorethamine 0.016%, samples were collected to measure mechlorethamine concentrations prior to dosing, on day 1, and at the first month visit. Following the topical administration of mechlorethamine 0.016%, there were no detectable plasma mechlorethamine concentrations observed in any of the patients. Patients who received mechlorethamine 0.032% had no measurable concentrations of mechlorethamine or half-mustard after 2, 4, or 6 months of treatment.

13 NONCLINICAL TOXICOLOGY

13.1 Carcinogenesis, Mutagenesis, Impairment of Fertility

Mechlorethamine was carcinogenic in mice when injected intravenously with four doses of 2.4 mg/kg (0.1% solution) at 2-week intervals with observations for up to 2 years. An increased incidence of thymic lymphomas and pulmonary adenomas was observed. Painting mechlorethamine on the skin of mice at a dose of 4 mg/kg for periods of up to 33 weeks resulted in squamous cell tumors in 9 of 33 mice.

Mechlorethamine was genotoxic in multiple genetic toxicology studies, which included mutations in the bacterial reverse mutation assay (Ames test) and chromosome aberrations in mammalian cells. Dominant lethal mutations were produced in ICR/Ha Swiss mice.

The reproductive effects of VALCHLOR have not been studied; however, published literature indicates that fertility may be impaired by systemically administered mechlorethamine. Mechlorethamine impaired fertility in the male rats at a daily dose of 0.25 to 0.5 mg/kg when given intravenously every two weeks for up to 12 doses. When mechlorethamine was administered intraperitoneally to male and female mice for 4 consecutive days at a dose of 0.5 mg/kg the pregnancy rate decreased (from 80% to 12.5%) when treated males were paired with treated females. Treatment with intravenous mechlorethamine has been associated with delayed catamenia, oligomenorrhea, and temporary or permanent amenorrhea.

13.2 Animal Toxicology and/or Pharmacology

Animal studies have shown mechlorethamine to be corrosive to skin and eyes, a powerful vesicant, irritating to the mucous membranes of the respiratory tract, and highly toxic by the oral route.

14 CLINICAL STUDIES

The efficacy of VALCHLOR was assessed in a randomized, multicenter, observer-blind, active-controlled, non-inferiority clinical trial of 260 patients with Stage IA, IB, and IIA mycosis fungoides-type cutaneous T-cell lymphoma (MF-CTCL) who had received at least one prior skin-directed therapy. Qualifying prior therapies included topical corticosteroids, phototherapy, Targretin® gel, and topical nitrogen mustard. Patients were not required to be refractory to or intolerant of prior therapies.

Patients were stratified based on Stage (IA vs. IB and IIA) and then randomized to receive VALCHLOR 0.016% (equivalent to 0.02% mechlorethamine HCl) or Aquaphor®-based mechlorethamine HCl 0.02% ointment (Comparator) at 13 centers in the United States. Eighteen patients were excluded from the efficacy analysis due to protocol violations involving randomization at a single site.

Study drug was to be applied topically on a daily basis for 12 months. Concomitant use of topical corticosteroids was not permitted during the study. Dosing could be suspended or continued with reduced frequency for dermatitis. The mean daily usage of VALCHLOR gel was 2.8 g (1 to 2 tubes per month). The maximum daily usage was 10.5 g (5 to 6 tubes per month).

Patients were evaluated for a response on a monthly basis for the first 6 months and then every 2 months for the last 6 months using the Composite Assessment of Index Lesion Severity (CAILS) score. The CAILS score is obtained by adding the severity score of each of the following categories for up to 5 index lesions: erythema, scaling, plaque elevation, and surface area. Severity was graded from 0 (none) to 8 (severe) for erythema and scaling; 0 to 3 for plaque elevation; and 0 to 9 for surface area. A response was defined as greater than or equal to 50% reduction in baseline CAILS score which was confirmed at the next visit at least 4 weeks later. A complete response was defined as a confirmed CAILS score of 0. Non-inferiority was considered to have been demonstrated if the lower bound of the 95% confidence interval (CI) around the ratio of response rates (VALCHLOR/Comparator) was greater than or equal to 0.75.

Patients were also evaluated using the Severity Weighted Assessment Tool (SWAT). The SWAT score is derived by measuring each involved area as a percentage of total body surface area (%BSA) and multiplying it by a severity weighting factor (1=patch, 2=plaque, 3=tumor or ulcer). A response was defined as greater than or equal to 50% reduction in baseline SWAT score which was confirmed at the next visit at least 4 weeks later.

The baseline demographics and disease characteristics were balanced between treatment arms. The median age was 57 years in the VALCHLOR arm and 58 years in the comparator arm. The majority of the patients were male (60% in VALCHLOR arm, 59% in Comparator arm) and white (75% in both treatment arms). The median number of prior therapies was 2 in both treatment arms. The most common prior therapy was topical corticosteroids (used in 86% of patients in both treatment arms). The median body surface area (BSA) involvement at baseline was 8.5% (range 1%, 61%) in the VALCHLOR arm and 9% (range 1%, 76%) in the comparator arm.

Sixty percent (60%) of the patients on the VALCHLOR arm and 48% of patients on the comparator arm achieved a response based on the CAILS score. VALCHLOR was non-inferior to the comparator based on a CAILS overall response rate ratio of 1.24 (95% CI 0.98, 1.58). Complete responses constituted a minority of the CAILS or SWAT overall responses (Table 2). The onset of CAILS overall response for both treatment arms showed a wide range from 1 to 11 months.

Table 2. Efficacy in Patients with Mycosis Fungoides-Type Cutaneous T-Cell Lymphoma (MF-CTCL)
Response Rates | VALCHLOR N=119 | Comparator N=123
CAILS Overall Response (CR+PR) Complete Response (CR) Partial Response (PR) | 60% 14% 45% | 48% 11% 37%
SWAT Overall Response (CR+PR) Complete Response (CR) Partial Response (PR) | 50% 7% 43% | 46% 3% 43%

15 REFERENCES

^1 OSHA Hazardous Drugs. OSHA. http://www.osha.gov/SLTC/hazardousdrugs/index.html

16 HOW SUPPLIED/STORAGE AND HANDLING

VALCHLOR is supplied in 60g tubes of 0.016% w/w mechlorethamine as a clear gel [NDC 69639-120-01].

STORAGE AND HANDLING

Prior to dispensing, store in the freezer at -13°F to 5°F (-25°C to -15°C). Advise patients that refrigerated storage is required once dispensed.

VALCHLOR is a cytotoxic drug. Follow applicable special handling and disposal procedures.^1

17 PATIENT COUNSELING INFORMATION

See FDA-approved patient labeling (Medication Guide)

Advise patients of the following and provide a copy of the Medication Guide.

Instructions for Patients and Caregivers for Application of VALCHLOR:
Apply a thin film of VALCHLOR once daily to affected areas of the skin [see Dosage and Administration (2.1)].

Patients must wash hands thoroughly with soap and water after handling or applying VALCHLOR. Caregivers must wear disposable nitrile gloves when applying VALCHLOR to patients and wash hands thoroughly with soap and water after removal of gloves. If there is accidental skin exposure to VALCHLOR, caregivers must immediately wash exposed areas thoroughly with soap and water and remove contaminated clothing [see Dosage and Administration (2.2)].

Patients and caregivers should follow these instructions when applying VALCHLOR [see Dosage and Administration (2.2)]:

- Apply immediately or within 30 minutes after removal from the refrigerator. Return VALCHLOR to the refrigerator immediately after each use.
- Apply VALCHLOR to completely dry skin at least 4 hours before or 30 minutes after showering or washing. Allow treated areas to dry for 5 to 10 minutes after application before covering with clothing.
- Emollients (moisturizers) may be applied to the treated areas 2 hours before or 2 hours after application of VALCHLOR.
- Occlusive (air or water-tight) dressings should not be used on areas of the skin where VALCHLOR was applied.

Instructions for Patients and Caregivers for Storage of VALCHLOR
Store VALCHLOR refrigerated at temperatures between 36°F - 46°F (2°C - 8°C). Advise patients that adherence to the recommended storage condition will ensure VALCHLOR will work as expected. Patients should consult a pharmacist prior to using VALCHLOR that has been left at room temperature for longer than one hour per day. Unused product should be discarded after 90 days [see How Supplied/Storage and Handling (16)].

With clean hands, replace tube in the original box, then place in the refrigerator. Keep VALCHLOR in its original box out of the reach of children and avoid contact with food when storing in the refrigerator.

Unused VALCHLOR, empty tubes, and used application gloves should be discarded in household trash in a manner that prevents accidental application or ingestion by others, including children and pets.

Mucosal or Eye Injury
Exposure of the eyes to mechlorethamine causes pain, burns, inflammation, photophobia, and blurred vision. Blindness and severe irreversible eye injury may occur. Should eye contact occur, immediately irrigate for at least 15 minutes with copious amounts of water, normal saline, or a balanced salt ophthalmic irrigating solution, followed by immediate ophthalmologic consultation [see Warnings and Precautions (5.1)].

Exposure of mucous membranes such as the oral mucosa or nasal mucosa causes pain, redness, and ulceration, which may be severe. Should mucosal contact occur, immediately irrigate for at least 15 minutes with copious amounts of water, followed by immediate medical consultation [see Warnings and Precautions (5.1)].

Secondary Exposure to VALCHLOR
Avoid direct skin contact with VALCHLOR in individuals other than the patient. Risks of secondary exposure include dermatitis, mucosal injury, and secondary cancers. Caregivers who help apply VALCHLOR to patients must wear disposable nitrile gloves when handling VALCHLOR. If secondary exposure occurs to eyes, mouth, or nose, immediately irrigate the exposed area for at least 15 minutes with copious amounts of water. Thoroughly wash affected areas of the skin with soap and water [see Dosage and Administration (2.2) and Warnings and Precautions (5.2)].

Dermatitis
If patients experience skin irritation after applying VALCHLOR, such as redness, swelling, inflammation, itchiness, blisters, ulceration, or secondary skin infections, instruct patients to discuss with their physician options for changes in the treatment plan. The face, genitalia, anus, or intertriginous skin (skin folds or creases) are at increased risk of skin irritation [see Warnings and Precautions (5.3)].

Non-Melanoma Skin Cancers
Instruct patients to notify their physician of any new skin lesions and to undergo periodic assessment for signs and symptoms of skin cancer. Non-melanoma skin cancers have been reported in patients receiving the active ingredient in VALCHLOR. Non-melanoma skin cancer may occur at multiple areas, including areas not directly treated with VALCHLOR [see Warnings and Precautions (5.4)].

Embryo-fetal Toxicity

Advise women of the potential risk to the fetus and to avoid pregnancy while using VALCHLOR. Advise males with female partners of reproductive potential to use a barrier method of contraception while using VALCHLOR [see Use in Specific Populations (8.1, 8.3)].

Lactation

Advise females not to breastfeed during treatment with VALCHLOR [see Use in Specific Populations (8.2)].

Manufactured for:
Helsinn Therapeutics, (U.S.), Inc., Iselin, NJ 08830

MEDICATION GUIDE
VALCHLOR ® (val-klor)
(mechlorethamine) gel

Important information: VALCHLOR is for use on skin only. Do not get VALCHLOR near or in your eyes, mouth, or nose.

What is the most important information I should know about VALCHLOR?
Keep VALCHLOR away from your eyes, mouth, and nose.

- If VALCHLOR gets in your eyes it can cause eye pain, burning, swelling, redness, sensitivity to light, and blurred vision. It may also cause blindness and permanent injury to your eyes. If VALCHLOR gets in your eyes, rinse your eyes right away for at least 15 minutes with a large amount of water, normal saline, or an eye wash solution.
- If VALCHLOR gets in your mouth or nose it can cause pain, redness, and ulcers. Rinse the affected area right away for at least 15 minutes with a large amount of water.

Get medical help right away if VALCHLOR gets in your eyes, mouth, or nose. Talk with your healthcare provider before using VALCHLOR about how to get medical help.

What is VALCHLOR?
VALCHLOR is a prescription medicine used on the skin (topical) to treat people with Stage 1A and 1B mycosis fungoides-type cutaneous T-cell lymphoma who have received previous skin treatment. It is not known if VALCHLOR is safe and effective in children.

Do not use VALCHLOR if you are severely allergic to mechlorethamine. Tell your healthcare provider if you have had an allergic reaction to mechlorethamine.

Before using VALCHLOR, tell your healthcare provider about all of your medical conditions, including if you:

- are pregnant or plan to become pregnant. VALCHLOR may harm your unborn baby. Avoid becoming pregnant during treatment with VALCHLOR. Tell your healthcare provider right away if you become pregnant while using VALCHLOR.

-Females who are able to become pregnant should use a barrier method of birth control, such as a male condom or spermicide, during treatment with VALCHLOR.

-Males with female partners who are able to become pregnant should use a barrier method of birth control, such as a male condom or spermicide, during treatment with VALCHLOR.

- are breastfeeding or plan to breastfeed. It is not known if VALCHLOR passes into your breast milk. Do not breastfeed during treatment with VALCHLOR.

Tell your healthcare provider about all the medicines you take including prescription and over-the-counter medicines, vitamins, and herbal supplements.

How should I use VALCHLOR?

- Use VALCHLOR exactly as your healthcare provider tells you.
- Caregivers must wear disposable nitrile gloves when applying VALCHLOR.
- Wash your hands with soap and water after touching or applying VALCHLOR.
- Safely throw away used disposable nitrile gloves in household trash.
- Apply VALCHLOR right away or within 30 minutes after you take it out of the refrigerator.
- Return VALCHLOR to the refrigerator right after each use.
- Apply a thin layer of VALCHLOR 1 time each day (or as instructed by your healthcare providers) to completely dry affected areas of the skin at least 4 hours before or 30 minutes after showering or washing.
- Let the treated areas dry for 5 to 10 minutes after applying VALCHLOR before covering with clothing.
- Moisturizers may be applied to the treated areas 2 hours before or 2 hours after applying VALCHLOR.
- You should not use air or water-tight bandages on areas of the skin treated with VALCHLOR.

What should I avoid while using VALCHLOR?
VALCHLOR is flammable. Avoid fire, flame, and smoking until VALCHLOR has dried.

What are the possible side effects of VALCHLOR?
See " What is the most important information I should know about VALCHLOR?"
VALCHLOR can cause serious side effects, including:

- Risk of Secondary Exposure to VALCHLOR. You may have a risk of inflammation of your skin (dermatitis), injury to your eyes, mouth, or nose, and certain types of cancers. Caregivers who accidentally come into contact with VALCHLOR must wash the affected area with soap and water right away for at least 15 minutes and remove any contaminated clothing.
  Get medical help right away if VALCHLOR gets in your eyes, mouth, or nose.
- Inflammation of your skin (dermatitis) is common with VALCHLOR and may sometimes be severe. Your risk for dermatitis is increased if VALCHLOR is applied to your face, genital area, anus, or skin folds. Tell your healthcare provider if you develop skin reactions such as redness, swelling, itching, blisters, ulcers, and skin infections.
- Increased risk of certain types of skin cancers. Certain types of skin cancer can develop on areas of your skin that are treated with VALCHLOR and areas of your skin that are not treated with VALCHLOR. Your healthcare provider will check your skin for skin cancers during and after your treatment with VALCHLOR. Tell your healthcare provider if you get any new skin lesions.

The most common side effects of VALCHLOR include: redness, swelling, itching, skin ulcers or blisters, skin infection, and darkening of areas of your skin.

VALCHLOR may cause fertility problems in females and males. This could affect the ability to become pregnant. Talk to your healthcare provider if this is a concern for you.

These are not all the possible side effects of VALCHLOR.
Call your doctor for medical advice about side effects. You may report side effects to FDA at 1-800-FDA-1088.

How should I store VALCHLOR?

- Store VALCHLOR in the refrigerator between 36°F to 46°F (2°C to 8°C).
- Keep VALCHLOR away from food in the refrigerator.
- With clean hands, place VALCHLOR back in the box it came in and return it to the refrigerator right after each use.
- Talk with your pharmacist before you use VALCHLOR that has been out of the refrigerator for more than one hour a day.
- Safely throw away VALCHLOR that is not used after 90 days. Unused VALCHLOR, empty tubes, and used disposable nitrile gloves should be safely thrown away in household trash.
- Keep VALCHLOR and all medicines out of the reach of children.

General information about the safe and effective use of VALCHLOR.
Medicines are sometimes prescribed for purposes other than those listed in a Medication Guide. Do not use VALCHLOR for a condition for which it was not prescribed. Do not give VALCHLOR to other people, even if they have the same symptoms that you have. It may harm them.
You can ask your healthcare provider or pharmacist for information about VALCHLOR that is written for health professionals.

What are the ingredients in VALCHLOR?
Active ingredient: mechlorethamine
Inactive ingredients: diethylene glycol monoethyl ether, propylene glycol, isopropyl alcohol, glycerin, lactic acid, hydroxypropylcellulose, sodium chloride, menthol, edetate disodium, butylated hydroxytoluene
Manufactured for: Helsinn Therapeutics (U.S.), Inc., Iselin, NJ 08830
For more information, go to www.VALCHLOR.com or call 1-855-482-5245.

This Medication Guide has been approved by the U.S. Food and Drug Administration. Revised: 01/2020

Principal Display Panel - 60 g Tube Carton

VALCHLOR®
(mechlorethamine) gel
0.016%

For Topical Use
Dispense with Medication Guide

Before dispensing, store in freezer
After dispensing, store refrigerated

RX Only
NET WT 60 grams

NDC 69639-120-01